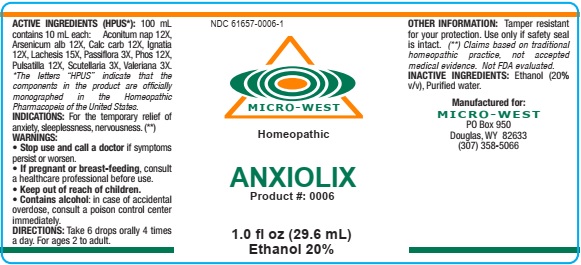 DRUG LABEL: Anxiolix
NDC: 61657-0006 | Form: LIQUID
Manufacturer: White Manufacturing Inc. DBA Micro West
Category: homeopathic | Type: HUMAN OTC DRUG LABEL
Date: 20210121

ACTIVE INGREDIENTS: ARSENIC TRIOXIDE 12 [hp_X]/30 mL; SCUTELLARIA LATERIFLORA 3 [hp_X]/30 mL; PHOSPHORUS 12 [hp_X]/30 mL; LACHESIS MUTA VENOM 15 [hp_X]/30 mL; PULSATILLA VULGARIS 12 [hp_X]/30 mL; PASSIFLORA INCARNATA FLOWERING TOP 3 [hp_X]/30 mL; ACONITUM NAPELLUS 12 [hp_X]/30 mL; VALERIAN 3 [hp_X]/30 mL; OYSTER SHELL CALCIUM CARBONATE, CRUDE 12 [hp_X]/30 mL; STRYCHNOS IGNATII SEED 12 [hp_X]/30 mL
INACTIVE INGREDIENTS: ALCOHOL

Drug Facts

ACTIVE INGREDIENTS

Aconitum nap 12X

Arsenicum alb 12X

Calc carb 12X

Ignatia 12X

Lachesis 15X

Passiflora 3X

Phosphorus 12X

Pulsitilla 12X

Scutellaria 3X

Valeriana 3X

INACTIVE INGREDIENT

Alcohol (2% v/v), Purified water

PURPOSE

TEMPORARY RELIEF OF ANXIETY, SLEEPLESSNESS, NERVOUSNESS

KEEP OUT OF REACH OF CHILDREN

INDICATIONS

INDICATIONS: FOR THE TEMPORARY RELIEF OF ANXIETY, SLEEPLESSNESS, NERVOUSNESS

WARNING

WARNING: Stop use and call a doctor if symptoms persist or worsen. If pregnant or breast feeding, consult a healthcare professional before use. Contains alcohol: in case of accidental overdose, consult a poison control center immediately.

DIRECTIONS

Directions: Take 6 drops orally, 4 times a day. For ages 2 to adult.

MANUFACTURE

MANUFACTURED FOR

MICRO-WEST

DOUGLAS, WY 82633

1-307-358-5066

INACTIVE INGREDIENT

Alcohol (20%, v/v)

PACKAGE LABEL

NDC 61657-0006-1

MICRO-WEST

Homepathic

ANXIOLIX

Product #: 0006

1.0 fl oz (29.6 mL)

Ethanol 20%